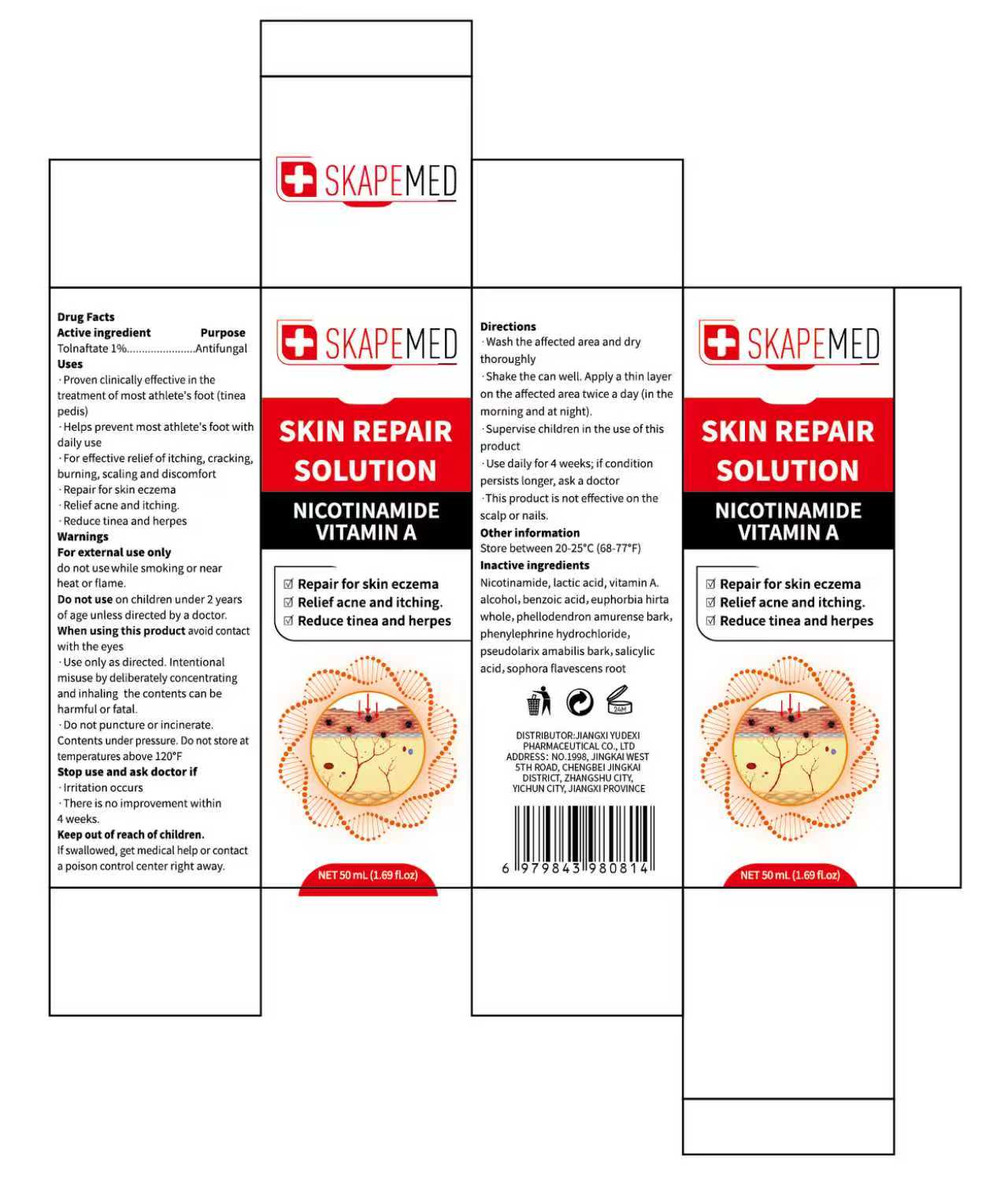 DRUG LABEL: SKAPEMED SKIN REPAIR
NDC: 85248-054 | Form: LIQUID
Manufacturer: Jiangxi Yudexi Pharmaceutical Co., LTD
Category: otc | Type: HUMAN OTC DRUG LABEL
Date: 20260205

ACTIVE INGREDIENTS: TOLNAFTATE 1 g/100 mL
INACTIVE INGREDIENTS: ALCOHOL; VITAMIN A; BENZOIC ACID; PHENYLEPHRINE HYDROCHLORIDE; NIACINAMIDE; SOPHORA FLAVESCENS ROOT; EUPHORBIA HIRTA WHOLE; PHELLODENDRON AMURENSE BARK; LACTIC ACID; SALICYLIC ACID

85248-054

Active Ingredient

Tolnaftate 1%

Purpose

Antifungal

Use

·Proven clinically effective in the treatment of most athlete's foot (tinea pedis) ·Helps prevent most athlete's foot with daily use ·For effective relief of itching, cracking, burning, scaling and discomfort
·Repair for skin eczema
·Relief acne and itching.
·Reduce tinea and herpes

Warnings

For external use only
Extremely Flammable do not use while smoking or near heat or flame. Do not use on children under 2 years of age unless directed by a doctor.When using this product avoid contact with the eyes ·Use only as directed.Intentional misuse by deliberately concentrating and inhaling the contents can be harmful or fatal .Do not puncture or incinerate. Contents under pressure. Do not store attemperatures above 120°F

Do not use

on children under 2 years of age unless directed by a doctor.

When Using

When using this product avoid contact with the eyes

Stop Use

·Irritation occurs
·There is no improvement within 4 weeks.

Ask Doctor

do not use while smoking or near heat or flame.Do not use on children under 2 years of age unless directed by a doctor.When using this product avoid contact with the eyes

Keep Oot Of Reach Of Children

If swallowed, get medical help or contact a poison control center right away.

Directions

·Wash the affected area and dry thoroughly ·Shake the can well. Apply a thin layer on the affected area twice a day (in the morning and at night). ·Supervise children in the use of this product ·Use daily for 4 weeks; if condition persists longer, ask a doctor ·This product is not effective on the scalp or nails.

Other information

Store between 20-25°C(68-77°F)

Inactive ingredients

Nicotinamide, lactic acid, vitamin A.alcohol, benzoic acid, euphorbia hirta whole,phellodendron amurense bark,phenylephrine hydrochloride, pseudol arix amabilis bark,salicylic acid,sophora flavescens root